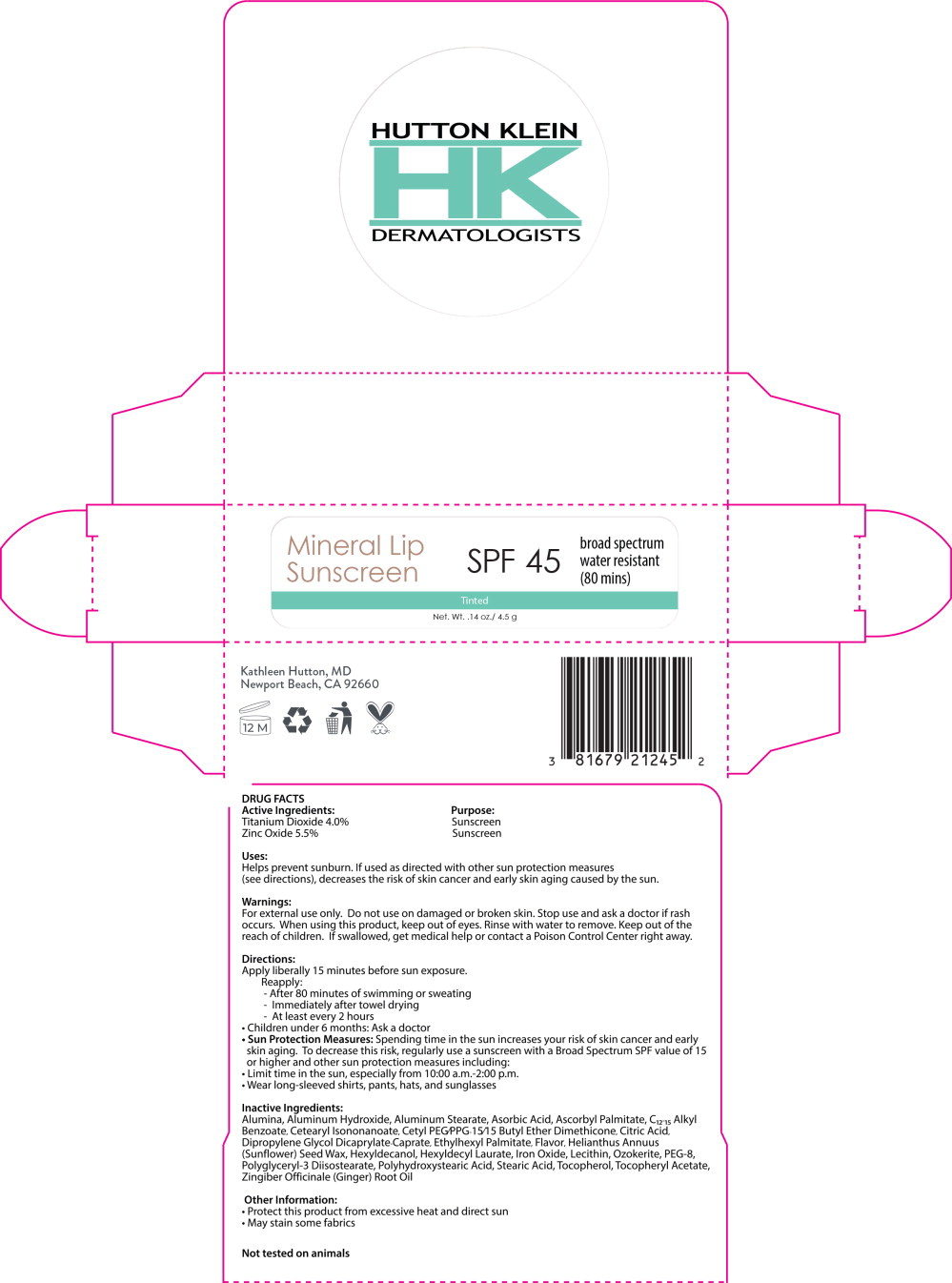 DRUG LABEL: Mineral Lip Sunscreen
NDC: 81679-212 | Form: STICK
Manufacturer: Hutton, Kathleen MD
Category: otc | Type: HUMAN OTC DRUG LABEL
Date: 20250116

ACTIVE INGREDIENTS: Titanium Dioxide 40 mg/1 g; Zinc Oxide 55 mg/1 g
INACTIVE INGREDIENTS: ALUMINUM OXIDE; ALUMINUM HYDROXIDE; ALUMINUM STEARATE; ASCORBIC ACID; ASCORBYL PALMITATE; ALKYL (C12-15) BENZOATE; CETEARYL ISONONANOATE; CETYL PEG/PPG-10/1 DIMETHICONE (HLB 4); CITRIC ACID MONOHYDRATE; DIPROPYLENE GLYCOL CAPRYLATE; ETHYLHEXYL PALMITATE; CITRUS AURANTIIFOLIA FRUIT OIL; KIWI FRUIT OIL; HELIANTHUS ANNUUS SEED WAX; HEXYLDECANOL; HEXYL LAURATE; FERRIC OXIDE RED; LECITHIN, SUNFLOWER; CERESIN; POLYETHYLENE GLYCOL 400; POLYGLYCERYL-3 DIISOSTEARATE; POLYHYDROXYSTEARIC ACID (2300 MW); STEARIC ACID; TOCOPHEROL; .ALPHA.-TOCOPHEROL ACETATE; GINGER OIL

DRUG FACTS

Active Ingredients:

Titanium Dioxide 4.0%

Zinc Oxide 5.5%

Purpose:

Sunscreen

Sunscreen

Uses:

Helps prevent sunburn. If used as directed with other sun protection measures (see directions), decreases the risk of skin cancer and early skin aging caused by the sun.

Warnings:

For external use only.

Do not use on damaged or broken skin.

Stop use and ask a doctor if rash occurs.

When using this product, keep out of eyes. Rinse with water to remove.

KEEP OUT OF REACH OF CHILDREN

Keep out of the reach of children. If swallowed, get medical help or contact a Poison Control Center right away.

Directions:

Apply liberally 15 minutes before sun exposure.

Reapply:

- After 80 minutes of swimming or sweating
- Immediately after towel drying
- At least every 2 hours

- Children under 6 months: Ask a doctor
- Sun Protection Measures: Spending time in the sun increases your risk of skin cancer and early skin aging. To decrease this risk, regularly use a sunscreen with a Broad Spectrum SPF value of 15 or higher and other sun protection measures including:
- Limit time in the sun, especially from 10:00 a.m.-2:00 p.m.
- Wear long-sleeved shirts, pants, hats, and sunglasses

Inactive Ingredients:

Alumina, Aluminum Hydroxide, Aluminum Stearate, Asorbic Acid, Ascorbyl Palmitate, C12-15 Alkyl Benzoate, Cetearyl Isononanoate, Cetyl PEG/PPG-15/15 Butyl Ether Dimethicone, Citric Acid, Dipropylene Glycol Dicaprylate-Caprate, Ethylhexyl Palmitate, Flavor, Helianthus Annuus (Sunflower) Seed Wax, Hexyldecanol, Hexyldecyl Laurate, Iron Oxide, Lecithin, Ozokerite, PEG-8, Polyglyceryl-3 Diisostearate, Polyhydroxystearic Acid, Stearic Acid, Tocopherol, Tocopheryl Acetate, Zingiber Officinale (Ginger) Root Oil

Other Information:

- Protect this product from excessive heat and direct sun
- May stain some fabrics

Not tested on animals

Principal Display Panel – 4.5 g Tube Label

HUTTON KLEIN

HK
DERMATOLOGISTS

Mineral Lip
Sunscreen

SPF 45

broad spectrum

water resistant

(80 mins)

Tinted

Net. Wt. .14 oz./ 4.5 g